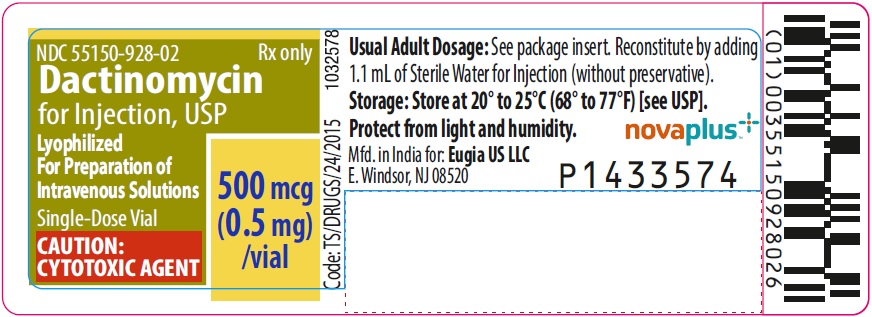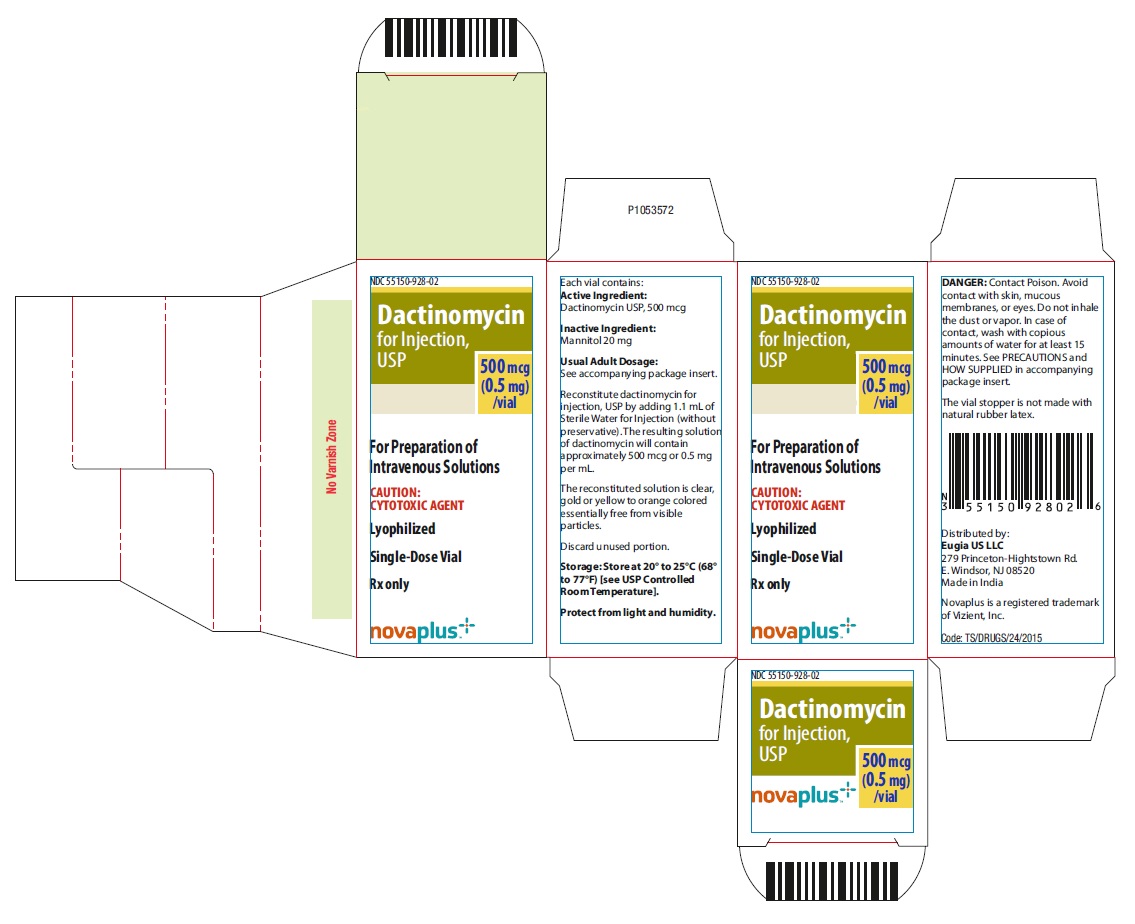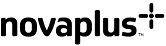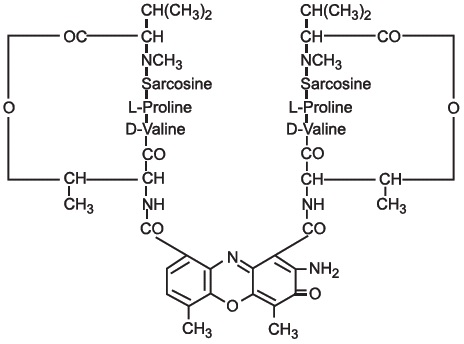 DRUG LABEL: DACTINOMYCIN
NDC: 55150-928 | Form: INJECTION, POWDER, LYOPHILIZED, FOR SOLUTION
Manufacturer: Eugia US LLC
Category: prescription | Type: Human Prescription Drug Label
Date: 20240618

ACTIVE INGREDIENTS: DACTINOMYCIN 0.5 mg/1 mL
INACTIVE INGREDIENTS: MANNITOL

HIGHLIGHTS OF PRESCRIBING INFORMATION

These highlights do not include all the information needed to use DACTINOMYCIN FOR INJECTION safely and effectively. See full prescribing information for DACTINOMYCIN FOR INJECTION.
DACTINOMYCIN for injection, for intravenous use
Initial U.S. Approval: 1964

1 INDICATIONS AND USAGE

Dactinomycin for injection is an actinomycin indicated for the treatment of:

- adult and pediatric patients with Wilms tumor, as part of a multi-phase, combination chemotherapy regimen. (1.1)
- adult and pediatric patients with rhabdomyosarcoma, as part of a multiphase, combination chemotherapy regimen. (1.2)
- adult and pediatric patients with Ewing sarcoma, as part of a multi-phase, combination chemotherapy regimen. (1.3)
- adult and pediatric patients with metastatic, nonseminomatous testicular cancer, as part of a multi-phase, combination chemotherapy regimen. (1.4)
- post-menarchal patients with gestational trophoblastic neoplasia, as a single agent or as part of a combination chemotherapy regimen. (1.5)
- adult patients with locally recurrent or locoregional solid malignancies, as a component of palliative or adjunctive regional perfusion. (1.6)

2 DOSAGE AND ADMINISTRATION

- Wilms Tumor: The recommended dose is 45 mcg/kg intravenously once every 3 to 6 weeks for up to 26 weeks, as part of a multi-agent combination chemotherapy regimen. (2.1)
- Rhabdomyosarcoma: The recommended dose is 15 mcg/kg intravenously once daily for 5 days every 3 to 9 weeks for up to 112 weeks, as part of a multi-agent combination chemotherapy regimen. (2.2)
- Ewing Sarcoma: The recommended dose is 1250 mcg/m^2 intravenously once every 3 weeks for 51 weeks, as part of a multi-agent combination chemotherapy regimen. (2.3)
- Metastatic Nonseminomatous Testicular Cancer: The recommended dose is 1000 mcg/m^2 intravenously every 3 weeks, as part of cisplatin-based, multi-drug chemotherapy regimen. (2.4)
- Gestational Trophoblastic Neoplasia:
  o Non-metastatic and Low-risk Metastatic Disease: The recommended dose is 12 mcg/kg intravenously daily for 5 days, as a single agent. (2.5)
  o High-risk Metastatic Disease: The recommended dose is 500 mcg intravenously on Days 1 and 2 every 2 weeks for up to 8 weeks, as part of a multi-agent combination chemotherapy regimen. (2.5)
- Regional Perfusion in Locally Recurrent and Locoregional Solid Malignancies:
  o Lower Extremity or Pelvis: The recommend dose is 50 mcg/kg once with melphalan. (2.6)
  o Upper Extremity: The recommended dose is 35 mcg/kg once with melphalan. (2.6)

3 DOSAGE FORMS AND STRENGTHS

For injection: 500 mcg as a lyophilized powder in a single-dose vial. (3)

4 CONTRAINDICATIONS

None. (4)

5 WARNINGS AND PRECAUTIONS

- Secondary Malignancy or Leukemia: Increased risk of secondary malignancies following treatment. (5.1)
- Veno-occlusive Disease: Can cause severe or fatal VOD. Monitor for elevations in AST, ALT, total bilirubin, hepatomegaly, weight gain, or ascites. Consider delaying next dose. (5.2)
- Extravasation: Immediately interrupt the injection or infusion and apply ice. (2.7, 5.3)
- Myelosuppression: Monitor blood cell counts before each cycle. Delay next dose if severe myelosuppression has not improved. (5.4)
- Immunizations: Vaccination with live viral vaccines is not recommended before or during treatment. (5.5)
- Severe Mucocutaneous Reactions: Discontinue treatment (5.6)
- Renal Toxicity: Monitor creatinine and electrolytes frequently. (5.7)
- Hepatotoxicity: Monitor transaminases, alkaline phosphatase and bilirubin prior to and during treatment. (5.8)
- Potentiation of Radiation Toxicity and Radiation Recall:
  Reduce dose by 50% during concomitant radiation. Use caution when administering within two months of radiation. (5.9)
- Embryo-fetal Toxicity: Can cause fetal harm. Advise patients of the potential risk to a fetus and to use effective contraception. (5.10, 8.1, 8.3)

6 ADVERSE REACTIONS

Common adverse reactions are: infection, alopecia, rash, dysphagia, fatigue, fever, nausea, vomiting, anemia, neutropenia, thrombocytopenia, mucositis, and hepatotoxicity (6)
To report SUSPECTED ADVERSE REACTIONS, contact Eugia US LLC at 1-866-850-2876 or FDA at 1-800-FDA-1088 or www.fda.gov/medwatch.

8 USE IN SPECIFIC POPULATIONS

- Lactation: Advise not to breastfeed. (8.2)

FULL PRESCRIBING INFORMATION

1 INDICATIONS AND USAGE

1.1 Wilms Tumor

Dactinomycin for injection is indicated for the treatment of adult and pediatric patients with Wilms tumor, as part of a multi-phase, combination chemotherapy regimen.

1.2 Rhabdomyosarcoma

Dactinomycin for injection is indicated for the treatment of adult and pediatric patients with rhabdomyosarcoma, as part of a multi-phase, combination chemotherapy regimen.

1.3 Ewing Sarcoma

Dactinomycin for injection is indicated for the treatment of adult and pediatric patients with Ewing sarcoma, as part of a multi-phase, combination chemotherapy regimen.

1.4 Metastatic Nonseminomatous Testicular Cancer

Dactinomycin for injection is indicated for the treatment of adult and pediatric patients with metastatic, nonseminomatous testicular cancer, as part of a multi-phase, combination chemotherapy regimen.

1.5 Gestational Trophoblastic Neoplasia

Dactinomycin for injection is indicated for the treatment of post-menarchal patients with gestational trophoblastic neoplasia, as a single agent or as part of a combination chemotherapy regimen.

1.6 Regional Perfusion in Locally Recurrent and Locoregional Solid Malignancies

Dactinomycin for injection is indicated for the treatment of adult patients with locally recurrent or locoregional solid malignancies, as a component of palliative or adjunctive regional perfusion.

2 DOSAGE AND ADMINISTRATION

2.1 Recommended Dosage for Wilms Tumor

The recommended dose of dactinomycin for injection, as part of a multi-agent combination chemotherapy regimen, is 45 mcg/kg intravenously once every 3 to 6 weeks for up to 26 weeks.

2.2 Recommended Dosage for Rhabdomyosarcoma

The recommended dose of dactinomycin for injection, as part of a multi-agent combination chemotherapy regimen, is 15 mcg/kg intravenously once daily for 5 days every 3 to 9 weeks for up to 112 weeks.

2.3 Recommended Dosage for Ewing Sarcoma

The recommended dose of dactinomycin for injection, as part of a multi-agent combination chemotherapy regimen, is 1,250 mcg/m^2 intravenously once every 3 weeks for 51 weeks.

2.4 Recommended Dosage for Metastatic Nonseminomatous Testicular Cancer

The recommended dose of dactinomycin for injection, as part of a cisplatin-based, multi-agent combination chemotherapy regimen, is 1,000 mcg/m^2 intravenously once every 3 weeks for 12 weeks.

2.5 Recommended Dosage for Gestational Trophoblastic Neoplasia

The recommended dose of dactinomycin for injection for nonmetastatic and low-risk metastatic disease is 12 mcg/kg intravenously daily for five days as a single agent.

The recommended dose of dactinomycin for injection, as part of a multi-agent combination chemotherapy regimen, for high-risk metastatic disease is 500 mcg intravenously on Days 1 and 2 every 2 weeks for up to 8 weeks.

2.6 Recommended Dosage for Regional Perfusion in Locally Recurrent and Locoregional Solid Malignancies

The recommended dose of dactinomycin for injection, in combination with melphalan, is 50 mcg/kg once for lower extremity or pelvis.
The recommended dose of dactinomycin for injection, in combination with melphalan, is 35 mcg/kg once for upper extremity.
Calculate the dose for obese or edematous patients based on ideal body weight.

2.7 Preparation and Administration

o Dactinomycin for injection is a cytotoxic drug. Follow applicable special handling and disposal procedures.^1
o Visually inspect the vials for particulate matter and discoloration, whenever solution and container permit.
Preparation
• Reconstitute each vial by adding 1.1 mL of Sterile Water for Injection without preservative using aseptic techniques.
• The reconstituted product should be a clear, gold-colored solution at a concentration of 500 mcg/mL.
• Further dilute the reconstituted product with 5% Dextrose Injection or 0.9% Sodium Chloride Injection to yield concentrations greater than 10 mcg/mL.
• Store at room temperature for no more than 4 hours from reconstitution to completion of injection or infusion. Discard after 4 hours.
• Dactinomycin for injection does not contain a preservative. Discard any unused portions.
Administration
• Administer the diluted reconstituted product intravenously over 10 to 15 minutes.
• Do not use in-line filters with a cellulose ester membrane.
Management of Extravasation
• Discontinue dactinomycin for injection for burning or stinging sensation or other evidence indicating perivenous infiltration or extravasation.
• Manage confirmed or suspected extravasation as follows:
o Terminate the injection or infusion immediately and restart in another vein.
o Intermittent application of ice to the site for 15 minutes 4 times daily for 3 days [see Warnings and Precautions (5.3)].

3 DOSAGE FORMS AND STRENGTHS

For injection: 500 mcg as a sterile, amorphous yellow to orange, lyophilized powder in a single-dose vial.

4 CONTRAINDICATIONS

None.

5 WARNINGS AND PRECAUTIONS

5.1 Secondary Malignancy or Leukemia

The risk of developing secondary malignancies, including leukemia, is increased following treatment with dactinomycin.

5.2 Veno-occlusive Disease

Severe and fatal hepatic veno-occlusive disease (VOD) can occur with dactinomycin. Risk factors for the development of VOD include age younger than 4 years or concomitant radiotherapy. After treatment with dactinomycin for injection, monitor frequently for signs and symptoms of VOD; these include elevations in AST, ALT, total bilirubin, hepatomegaly, weight gain, or ascites. If patients develop VOD, considering delaying next dose of dactinomycin. Resume, reduce dose or permanently discontinue based on severity of reaction and disease being treated.

5.3 Extravasation

Extravasation of dactinomycin for injection can result in severe local tissue injury manifesting as blistering, ulcerations and persistent pain requiring wide excision surgery followed by split-thickness skin grafting. If any signs or symptoms of extravasation occur, immediately interrupt the injection or infusion. Apply ice to the site intermittently for 15 minutes, 4 times a day for 3 days [see Dosage and Administration (2.7)]. Observe closely and consult plastic surgery if necessary based on severity of reaction.

5.4 Myelosuppression

Severe and fatal myelosuppression, which may include neutropenia, thrombocytopenia and anemia, can occur with dactinomycin for injection. The nadir in neutrophil counts generally occurs 14 to 21 days after administration. Obtain complete blood counts prior to each treatment cycle. Delay next dose of dactinomycin for injection if severe myelosuppression has not improved. Consider dose reduction for patients with prolonged myelosuppression based on severity of reaction and disease being treated.

5.5 Immunizations

The safety with live viral vaccines following dactinomycin for injection has not been studied and vaccination with live virus vaccines is not recommended before or during treatment.

5.6 Severe Mucocutaneous Reactions

Severe mucocutaneous reactions, such as Steven-Johnson syndrome and Toxic Epidermal Necrolysis (TEN), can occur with dactinomycin for injection. Permanently discontinue dactinomycin for injection in patients who experience a severe mucocutaneous reaction.

5.7 Renal Toxicity

Abnormalities of renal function can occur with dactinomycin for injection. Monitor creatinine and electrolytes frequently during dactinomycin for injection therapy.

5.8 Hepatotoxicity

Hepatotoxicity can occur with dactinomycin for injection. Monitor AST, ALT, alkaline phosphatase, and bilirubin prior to and during dactinomycin for injection therapy.

5.9 Potentiation of Radiation Toxicity and Radiation Recall

Dactinomycin for injection can increase radiation-induced gastrointestinal toxicity, myelosuppression, or erythema and vesiculation of the skin or buccal and pharyngeal mucosa. Reduce the dose of dactinomycin for injection by 50% during concomitant radiation.

Radiation recall, affecting previously treated radiation fields, can occur in patients who receive dactinomycin for injection after prior radiation therapy. Although the risk can occur with distant radiation exposure, the risk appears highest when dactinomycin for injection is administered within two months of prior radiation.

5.10 Embryo-Fetal Toxicity

Based on findings from animal studies and its mechanism of action, dactinomycin for injection can cause fetal harm when administered to a pregnant woman. In animal reproduction studies, administration of dactinomycin to pregnant animals during the period of organogenesis was teratogenic, resulting in malformations at doses lower than the recommended human dose.

Advise pregnant women of the potential risk to the fetus. Advise females of reproductive potential to use effective contraception during treatment with dactinomycin for injection and for at least 6 months after the final dose. Advise males with female partners of reproductive potential to use effective contraception during treatment with dactinomycin for injection and for 3 months after the final dose [see Use in Specific Populations (8.1, 8.3)].

6 ADVERSE REACTIONS

The following serious adverse reactions are described elsewhere in the labeling:
• Secondary Malignancy and Leukemia [see Warnings and Precautions (5.1)]
• Veno-occlusive Disease [see Warnings and Precautions (5.2)]
• Extravasation [see Warnings and Precautions (5.3)]
• Myelosuppression [see Warnings and Precautions (5.4)]
• Immunizations [see Warning and Precautions (5.5)]
• Severe Mucocutaneous Reactions [see Warnings and Precautions (5.6)]
• Renal Toxicity [see Warnings and Precautions (5.7)]
• Hepatotoxicity [see Warnings and Precautions (5.8)]
• Potentiation of Radiation Toxicity and Radiation Recall [see Warnings and Precautions (5.9)]
Common adverse reactions are: infection, alopecia, rash, dysphagia, fatigue, fever, nausea, vomiting, anemia, neutropenia, thrombocytopenia, mucositis, and hepatotoxicity.
The following adverse reactions have been identified in clinical studies or postmarketing reports.
Because some of these reactions were reported voluntarily from a population of uncertain size, it is not always possible to reliably estimate their frequency or establish a causal relationship to drug exposure.
Infections: infections including sepsis with fatal outcome
Hematologic: anemia, leukopenia, thrombocytopenia, pancytopenia, reticulocytopenia, neutropenia, febrile neutropenia, disseminated intravascular coagulation
Immune system: hypersensitivity
Metabolism and nutrition: anorexia, hypocalcemia, tumor lysis syndrome
Nervous system: peripheral neuropathy
Ocular: optic neuropathy
Vascular: thrombophlebitis, hemorrhage
Respiratory, thoracic and mediastinal: pneumonitis, pneumothorax
Gastrointestinal: nausea, vomiting, abdominal pain, diarrhea, constipation, gastrointestinal ulceration, cheilitis, dysphagia, esophagitis, ulcerative stomatitis, ascites, proctitis, mucositis
Hepatobiliary: liver function test abnormalities, hepatomegaly, hepatitis, hepatic failure with reports of death, hepatic veno-occlusive disease
Dermatologic: alopecia, rash, dermatitis, acne, erythema multiforme, Stevens Johnson Syndrome, radiation recall, toxic epidermal necrolysis
Musculoskeletal and connective tissue: myalgia, growth retardation
Renal and urinary: renal impairment, renal failure
General: fatigue, fever, malaise

8 USE IN SPECIFIC POPULATIONS

8.1 Pregnancy

Risk Summary

Based on findings from animal studies and its mechanism of action dactinomycin can cause fetal harm when administered to a pregnant woman [see Clinical Pharmacology (12.1)]. In animal reproduction studies, administration of dactinomycin to pregnant animals during the period of organogenesis was teratogenic, resulting in malformations at doses lower than the recommended human dose (see Data). Advise pregnant women of the potential risk to a fetus [see Use in Special Populations (8.3)].
In the U.S. general population, the estimated background risk of major birth defects and miscarriage in clinically recognized pregnancies is 2% to 4% and 15% to 20%, respectively.
Data
Animal Data
Dactinomycin was teratogenic in animals. Administration of dactinomycin to pregnant rats, rabbits, and hamsters during the period of organogenesis, increased the incidence of fetal malformations and caused embryotoxicity at doses (based on body surface area) as low as 0.2 times the clinical dose of 1,250 mcg/m^2.

8.2 Lactation

Risk Summary
There are no data on the presence of dactinomycin or its metabolites in human milk or their effects on the breastfed infant or on milk production. Because of the potential for serious adverse reactions in breastfed infants from dactinomycin, advise women not to breastfeed during treatment with dactinomycin for injection and, based on limited published data regarding the dactinomycin half-life, for 14 days after the final dose.

8.3 Females and Males of Reproductive Potential

Pregnancy Testing
Verify the pregnancy status of females of reproductive potential prior to initiating dactinomycin [see Use in Specific Population (8.1)].
Contraception
Dactinomycin can cause fetal harm when administered to a pregnant woman [see Use in Specific Populations (8.1)].
Females
Advise females of reproductive potential to use effective contraception during treatment with dactinomycin and for at least 6 months after the final dose.
Males
Because of the potential for genotoxicity, advise males with female partners of reproductive potential to use effective contraception during treatment with dactinomycin and for 3 months after the final dose [see Nonclinical Toxicology (13.1)].

8.4 Pediatric Use

The safety and effectiveness of dactinomycin have been established in pediatric patients with Wilms tumor, rhabdomyosarcoma, Ewing sarcoma, and metastatic nonseminomatous testicular cancer.
The safety and effectiveness of dactinomycin have been established in post-menarchal pediatric patients with gestational trophoblastic neoplasia.
The safety and effectiveness of dactinomycin have not been established in pediatric patients undergoing regional perfusion for locally recurrent or locoregional solid malignancies.

8.5 Geriatric Use

Clinical studies of dactinomycin did not include sufficient numbers of subjects aged 65 and over to determine whether they respond differently from younger subjects.

11 DESCRIPTION

Dactinomycin USP is one of the actinomycins, a group of antibiotics produced by various species of Streptomyces. Dactinomycin USP is the principal component of the mixture of actinomycins produced by Streptomyces parvullus. Unlike other species of Streptomyces, this organism yields an essentially pure substance that contains only traces of similar compounds differing in amino acid content of the peptide side chains. The empirical formula is C62H86N12O16 and the structural formula is:

Dactinomycin for Injection, USP is a sterile, yellow to orange, lyophilized powder for injection by intravenous route or by regional perfusion after reconstitution. Each vial contains 0.5 mg (500 mcg) of dactinomycin USP and 20 mg of mannitol.

12 CLINICAL PHARMACOLOGY

12.1 Mechanism of Action

Dactinomycin is a cytotoxic actinomycin that binds DNA and inhibits RNA synthesis. The cytotoxic activity of dactinomycin has been demonstrated in animal models of different human cancers.

12.2 Pharmacodynamics

Dactinomycin exposure-response relationships and the time course of pharmacodynamics response are unknown.

12.3 Pharmacokinetics

The distribution and excretion of radiolabeled dactinomycin (^3H actinomycin D) were assessed in three adult patients with malignant melanoma.
Distribution
^3H actinomycin D is concentrated in nucleated cells and does not penetrate the blood-brain barrier.
Elimination
Excretion
Following administration of radiolabeled dactinomycin, approximately 30% was recovered in urine and feces in one week.
Specific Populations
Pediatric Patients
Published studies and population analyses in patients ≤ 21 years of age with cancer report a trend of increasing systemic dactinomycin clearance with increasing body weight.
Drug Interaction Studies
Published in vitro studies report that dactinomycin may be a substrate of the P-glycoprotein and OATP1B3 transporter systems.

13 NONCLINICAL TOXICOLOGY

13.1 Carcinogenesis, Mutagenesis, Impairment of Fertility

Dactinomycin is a carcinogen in animals. Local sarcomas were produced in mice and rats after repeated subcutaneous or intraperitoneal injections. Mesenchymal tumors occurred in male rats given intraperitoneal injections of 50 mcg/kg, 2 to 5 times per week, for 18 weeks, at doses(based on body surface area) 0.5 times the clinical dose of 1,250 mcg/m^2.
Dactinomycin was mutagenic in several in vitro and in vivo test systems including human fibroblasts and leukocytes, and HeLa cells. DNA damage and cytogenetic effects have been demonstrated in the mouse and the rat.

15 REFERENCES

1. "OSHA Hazardous Drugs." OSHA. http://www.osha.gov/SLTC/hazardousdrugs/index.html

16 HOW SUPPLIED/STORAGE AND HANDLING

Dactinomycin for injection, USP is a lyophilized powder. In the dry form the compound is an amorphous yellow to orange powder. The solution is clear, gold or yellow to orange colored and essentially free from visible particles. Dactinomycin for injection, USP is supplied in vials containing 0.5 mg (500 micrograms) of dactinomycin USP and 20.0 mg of mannitol.
NDC 55150-928-02: 0.5 mg/vial in 2 mL single-dose vial; individually boxed
Storage: Store at 20º to 25ºC (68º to 77ºF); [see USP Controlled Room Temperature]. Protect from light and humidity.
Special Handling: Animal studies have shown dactinomycin to be corrosive to skin, irritating to the eyes and mucous membranes of the respiratory tract and highly toxic by the oral route. It has also been shown to be carcinogenic, mutagenic, embryotoxic and teratogenic. Due to the drug’s toxic properties, appropriate precautions including the use of appropriate safety equipment are recommended for the preparation of dactinomycin for injection for parenteral administration. Inhalation of dust or vapors and contact with skin or mucous membranes, especially those of the eyes, must be avoided. Avoid exposure during pregnancy. The National Institutes of Health presently recommends that the preparation of injectable antineoplastic drugs should be performed in a Class II laminar flow biological safety cabinet. Personnel preparing drugs of this class should wear chemical resistant, impervious gloves, safety goggles, outer garments and shoe covers. Additional body garments should be used based upon the task being performed (e.g., sleevelets, apron, gauntlets, disposable suits) to avoid exposed skin surfaces and inhalation of vapors and dust. Appropriate techniques should be used to remove potentially contaminated clothing.
Several other guidelines for proper handling and disposal of antineoplastic drugs have been published and should be considered.^1-4
Accidental Contact Measures: Should accidental eye contact occur, copious irrigation for at least 15 minutes with water, normal saline or a balanced salt ophthalmic irrigating solution should be instituted immediately, followed by prompt ophthalmologic consultation. Should accidental skin contact occur, the affected part must be irrigated immediately with copious amounts of water for at least 15 minutes while removing contaminated clothing and shoes. Medical attention should be sought immediately. Contaminated clothing should be destroyed and shoes cleaned thoroughly before reuse (see PRECAUTIONS, General and DOSAGE AND ADMINISTRATION, Preparation of Solution for Intravenous Administration).
The vial stopper is not made with natural rubber latex.

17 PATIENT COUNSELING INFORMATION

Secondary Malignancy or Leukemia
Advise patients of the increased risk of secondary malignancies [see Warnings and Precautions (5.1)].
Veno-occlusive Disease
Advise patients about the symptoms of VOD and to seek medical attention if they develop new onset jaundice, abdominal distention, or right upper quadrant pain [see Warnings and Precautions (5.2)].
Myelosuppression
Advise patients to contact their healthcare provider for any signs or symptoms of myelosuppression or infection [see Warnings and Precautions (5.4)].
Severe Mucocutaneous Reactions
Advise patients of the risk of severe mucocutaneous reactions and to contact their health care provided for new skin lesions, mouth sores or oropharyngeal lesions [see Warnings and Precautions (5.5)].
Renal Toxicity or Hepatotoxicity
Advise patients of the need for periodic laboratory testing to monitor for renal toxicity and hepatotoxicity [see Warnings and Precautions (5.7, 5.8)].
Potentiation of Radiation Toxicity and Radiation Recall
Advise patients of the risk of increased radiation-induced gastrointestinal, myelosuppression and skin toxicity [see Warnings and Precautions (5.9)].
Embryo-Fetal Toxicity
Advise females of reproductive potential of the potential risk to a fetus. Advise females to inform their healthcare provider of a known or suspected pregnancy [see Warnings and Precautions (5.10), Use in Specific Populations (8.1)].
Advise females of reproductive potential to use effective contraception during treatment with dactinomycin and for 6 months after final dose [see Use in Specific Populations (8.3)].
Advise male patients with female partners of reproductive potential to use effective contraception during treatment with dactinomycin and for 3 months after final dose [see Use in Specific Populations (8.3)].
Lactation
Advise females not to breastfeed during treatment with dactinomycin and for 14 days after the final dose [see Use in Specific Populations (8.2)].
Distributed by:
Eugia US LLC
279 Princeton-Hightstown Rd.
E. Windsor, NJ 08520
Manufactured by:
Eugia Pharma Specialities Limited
Hyderabad - 500032
India
Revised: October 2023

Novaplus is a registered trademark of Vizient Inc.

PACKAGE LABEL.PRINCIPAL DISPLAY PANEL-500 mcg (0.5 mg)/vial - Container Label

NDC 55150-928-02 Rx only
Dactinomycin
for Injection, USP
500 mcg (0.5 mg)/vial
Lyophilized
For Preparation of
Intravenous Solutions
Single-Dose Vial
CAUTION:
CYTOTOXIC AGENT

PACKAGE LABEL-PRINCIPAL DISPLAY PANEL-500 mcg (0.5 mg)/vial - Container-Carton

NDC 55150-928-02
Dactinomycin
for Injection, USP
500 mcg (0.5 mg)/vial
For Preparation of
Intravenous Solutions
CAUTION:
CYTOTOXIC AGENT
Lyophilized
Single-Dose Vial
Rx only
NOVAPLUS^+